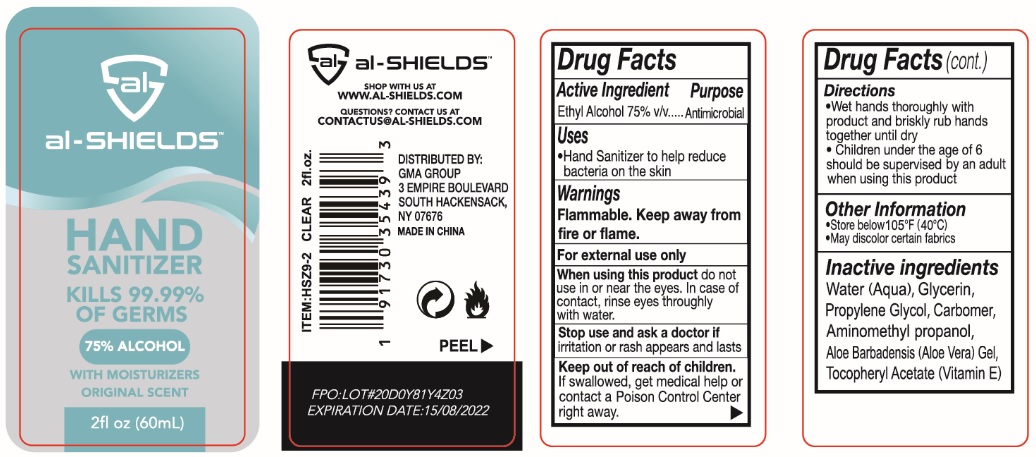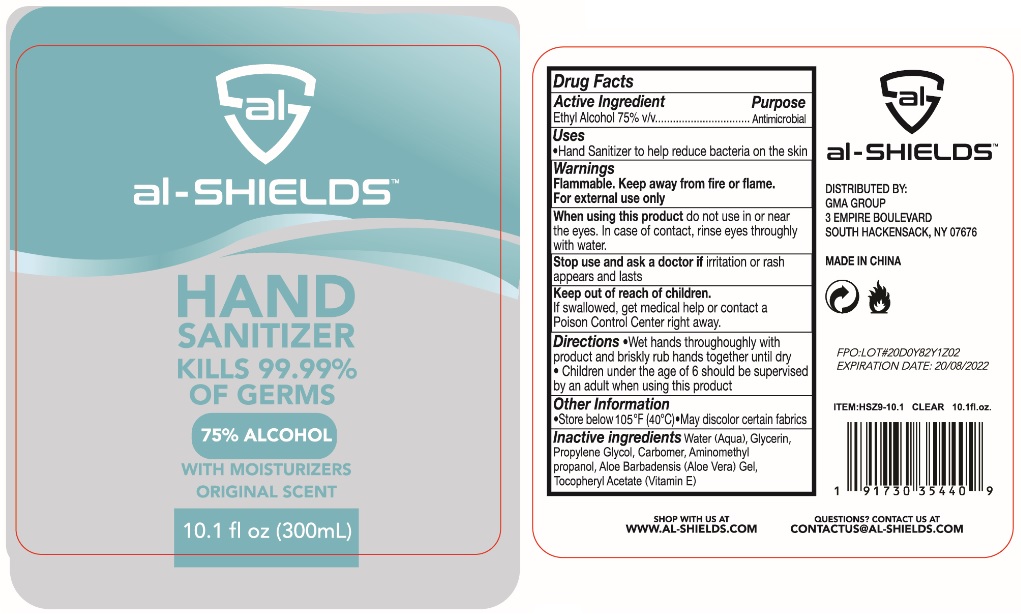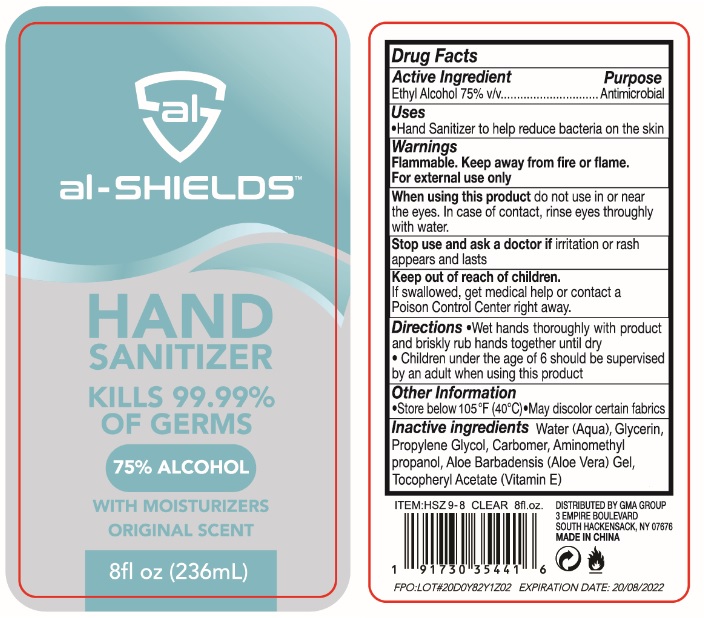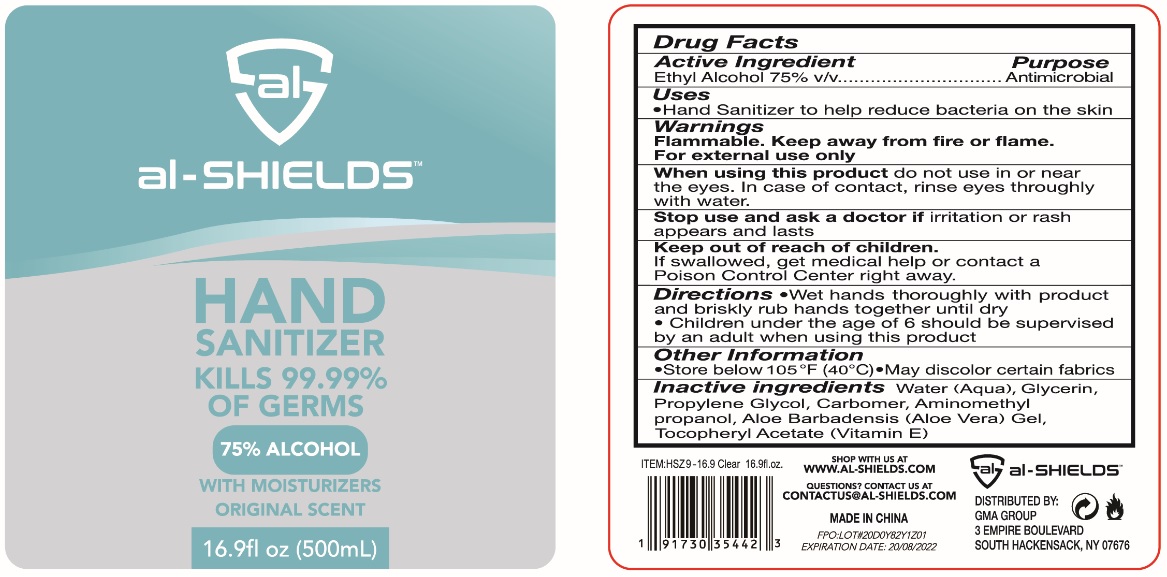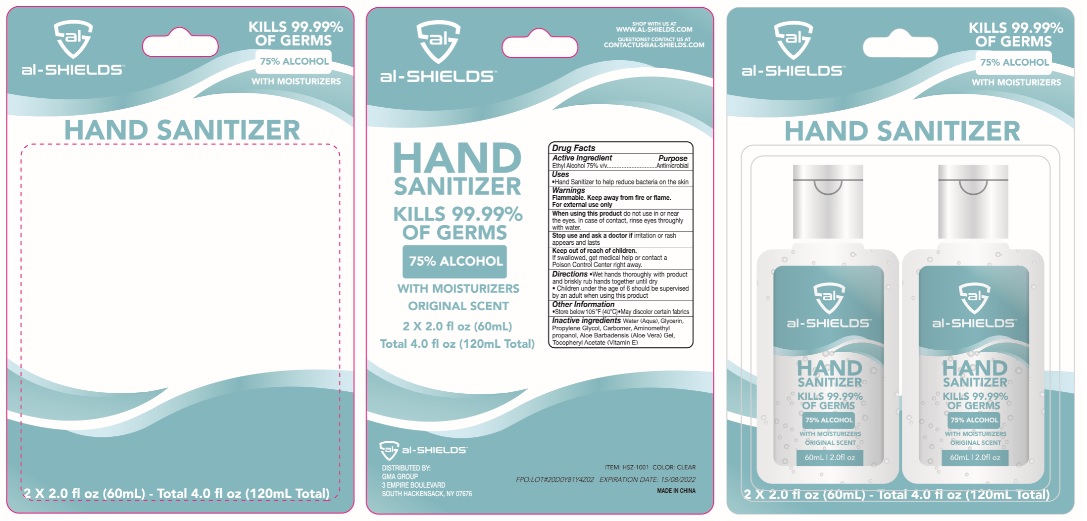 DRUG LABEL: al-SHIELDS
NDC: 72285-011 | Form: GEL
Manufacturer: Yozzi Co.,ltd
Category: otc | Type: HUMAN OTC DRUG LABEL
Date: 20220727

ACTIVE INGREDIENTS: ALCOHOL 75 mL/100 mL
INACTIVE INGREDIENTS: WATER; GLYCERIN; PROPYLENE GLYCOL; CARBOMER HOMOPOLYMER, UNSPECIFIED TYPE; AMINOMETHYLPROPANOL; ALOE VERA LEAF; .ALPHA.-TOCOPHEROL ACETATE

al-SHIELDS™ HAND SANITIZER

Active Ingredient

Ethyl Alcohol 75% v/v

Purpose

Antimicrobial

Uses

• Hand Sanitizer to help reduce bacteria on the skin

Warnings

Flammable. Keep away from fire or flame.

For external use only

When using this product do not use in or near the eyes. In case of contact, rinse eyes thoroughly with water.

Stop use and ask a doctor if irritation or rash appears and lasts

Keep out of reach of children.

If swallowed, get medical help or contact a Poison Control Center right away.

Directions

- Wet hands thoroughly with product and briskly rub hands together until dry
- Children under the age of 6 should be supervised by an adult when using this product

Other Information

- Store below 105°F (40°C)
- May discolor certain fabrics

Inactive ingredients

Water (Aqua), Glycerin, Propylene Glycol, Carbomer, Aminomethyl propanol Aloe Barbadensis (Aloe Vera) Gel, Tocopheryl Acetate (Vitamin E)

KILLS 99.99% OF GERMS

75% ALCOHOL

WITH MOISTURIZERS

ORIGINAL SCENT

SHOP WITH US AT

WWW.AL-SHIELDS.COM

QUESTIONS? CONTANT US AT

CONTACTUS@AL-SHIELDS.COM

DISTRIBUTED BY:

GMA GROUP

3 EMPIRE BOULEVARD

SOUTH HACKENSACK,

NY07676

MADE IN CHINA